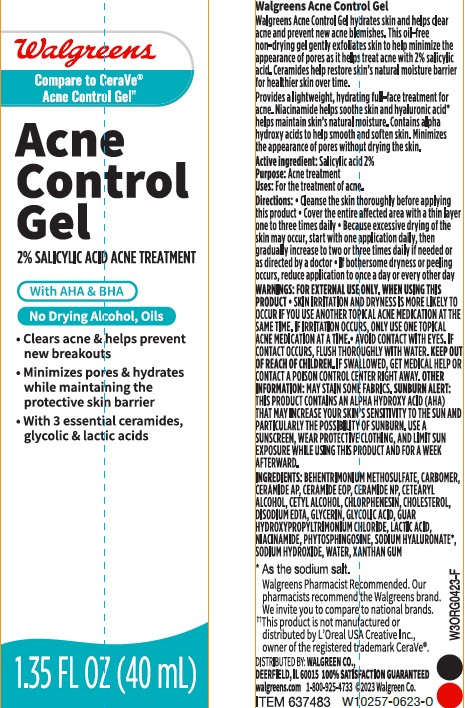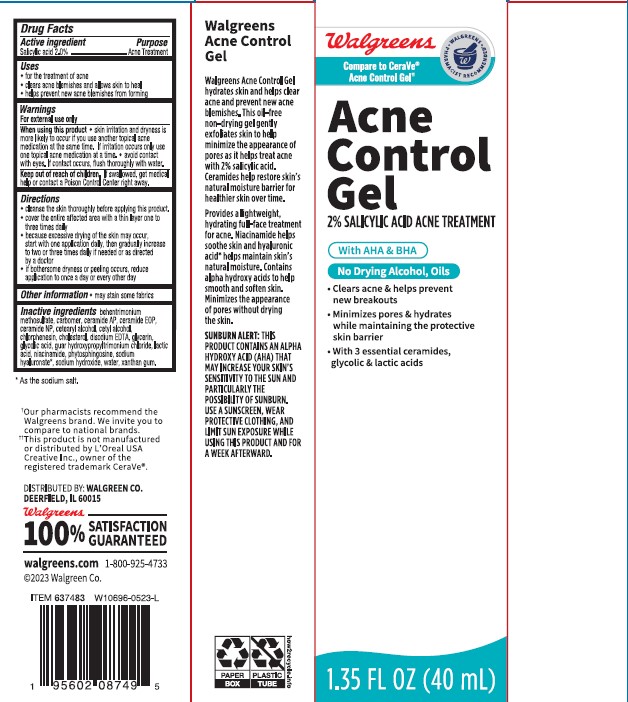 DRUG LABEL: Walgreens Acne Control Gel
NDC: 0363-0269 | Form: GEL
Manufacturer: WALGREEN COMPANY
Category: otc | Type: HUMAN OTC DRUG LABEL
Date: 20241014

ACTIVE INGREDIENTS: SALICYLIC ACID 20 mg/1 mL
INACTIVE INGREDIENTS: XANTHAN GUM; GLYCERIN; WATER; CHLORPHENESIN; CHOLESTEROL; GLYCOLIC ACID; GUAR HYDROXYPROPYLTRIMONIUM CHLORIDE (1.7 SUBSTITUENTS PER SACCHARIDE); LACTIC ACID; PHYTOSPHINGOSINE; HYALURONATE SODIUM; SODIUM HYDROXIDE; CETYL ALCOHOL; SODIUM LAUROYL LACTYLATE; CETOSTEARYL ALCOHOL; NIACINAMIDE; BEHENTRIMONIUM METHOSULFATE; CERAMIDE AP; POLYACRYLIC ACID (8000 MW); CERAMIDE NP; EDETATE DISODIUM

Walgreens Acne Control Gel

Active ingredient

Salicylic acid 2.0%

Purpose

Acne Treatment

Uses

- For the treatment of acne
- clears acne blemishes and allows skin to heal
- helps prevent new acne blemishes from forming

Warnings

For external use only

When using this product

- skin irritation and dryness is more likely to occur if you use another topical acne medication at the same time. If irritation occurs, only use one topical acne medication at a time.
- avoid contact with eyes. If contact occurs, flush thoroughly with water.

Keep out of reach of children.

If swallowed, get medical help or contact a Poison Control Center right away.

Directions

- cleanse the skin thoroughly before applying this product.
- cover the entire affected area with a thin layer one to three times daily.
- because excessive drying of the skin may occur, start with one application daily, then gradually increase to two or three times daily if needed or as directed by a doctor
- if bothersome dryness or peeling occurs, reduce application to once a day or every other day.

Other information

- may stain some fabrics

Inactive ingredients

behentrimonium methosulfate, carbomer, ceramide AP, ceramide EOP, ceramide NP, cetearyl alcohol, cetyl alcohol, chlorphenesin, cholesterol, disodium EDTA, glycerin, glycolic acid, guar hydroxypropyltrimonium chloride, lactic acid, niacinamide, phytosphingosine, sodium hyaluronate, sodium hydroxide, sodium lauroyl lactylate, water, xanthan gum